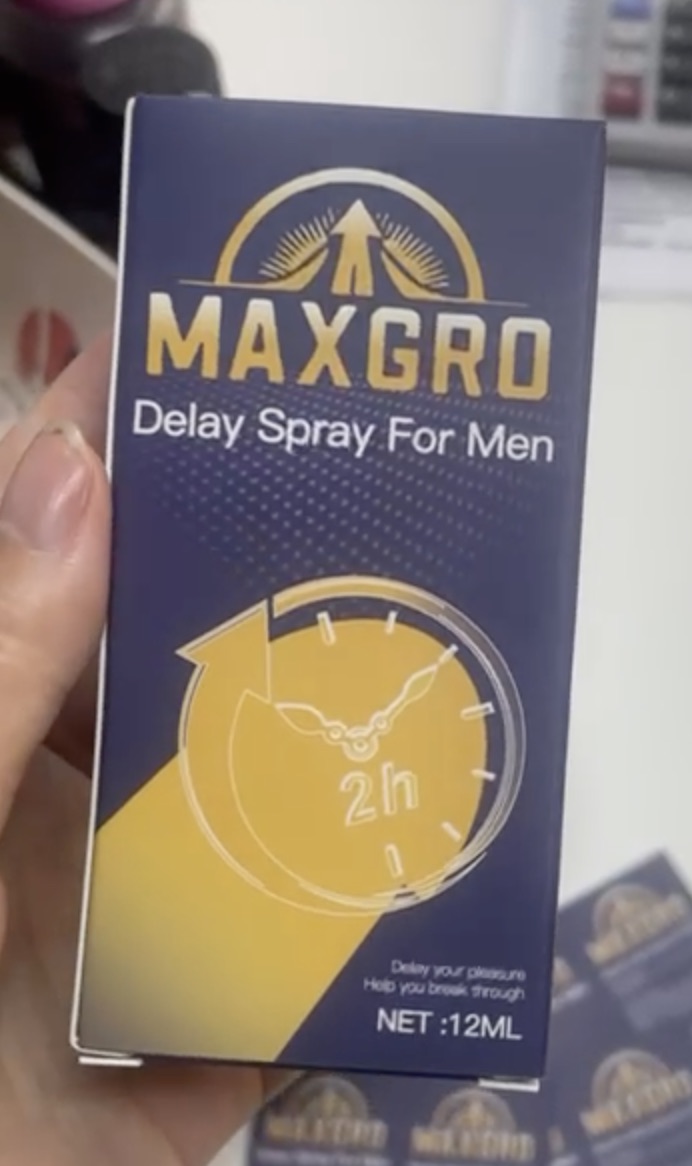 DRUG LABEL: MaxGro
NDC: 87187-0001 | Form: AEROSOL, SPRAY
Manufacturer: CJH Innovations LLC
Category: otc | Type: HUMAN OTC DRUG LABEL
Date: 20251117

ACTIVE INGREDIENTS: LIDOCAINE 10 mg/1 1
INACTIVE INGREDIENTS: IODOPROPYNYL BUTYLCARBAMATE; WATER; FD&C YELLOW NO. 5; ALCOHOL; PROPYLENE GLYCOL; METHYLISOTHIAZOLINONE; ANHYDROUS CITRIC ACID; FD&C YELLOW NO. 6

Dosage & administration

Gently shake bottle. Hold upright and press pump until spray dispenses. Apply 3 or more sprays, not to exceed 10, to head and shaft of penis 5-15 minutes before intercourse or use as directed by a doctor. Wash product off after intercourse.

Warnings

For external use only

Do not use
■ in the eyes
■ over large areas of the body
■ if allergic to any ingredient in this product
■ more than 1 week unless directed by a doctor

Ask a doctor before use if you have
■ any concerns about using this product

When using this product
■ avoid contact with the eyes

Stop use and ask a doctor if
■ condition worsens
■ symptoms persist for more than 7 days
■ symptoms clear up and occur again within a few days

Premature ejaculation may be due to a condition requiring medical supervision. If this product, used as directed, does not provide relief, discontinue use and consult a doctor.

Inactive ingredients

alcohol, citric acid, FD&C yellow no. 5, FD&C yellow no. 6, iodopropynyl butylcarbamate, methylisothiazolinone, nonylphenol ethoxylate, propylene glycol, water

Uses

helps in temporarily slowing the onset of ejaculation

Keep out of reach of children. If swallowed, get medical help or contact a Poison Control Center right away.

Purpose

Male Genital Desensitizer

label.jpg

label.jpeg